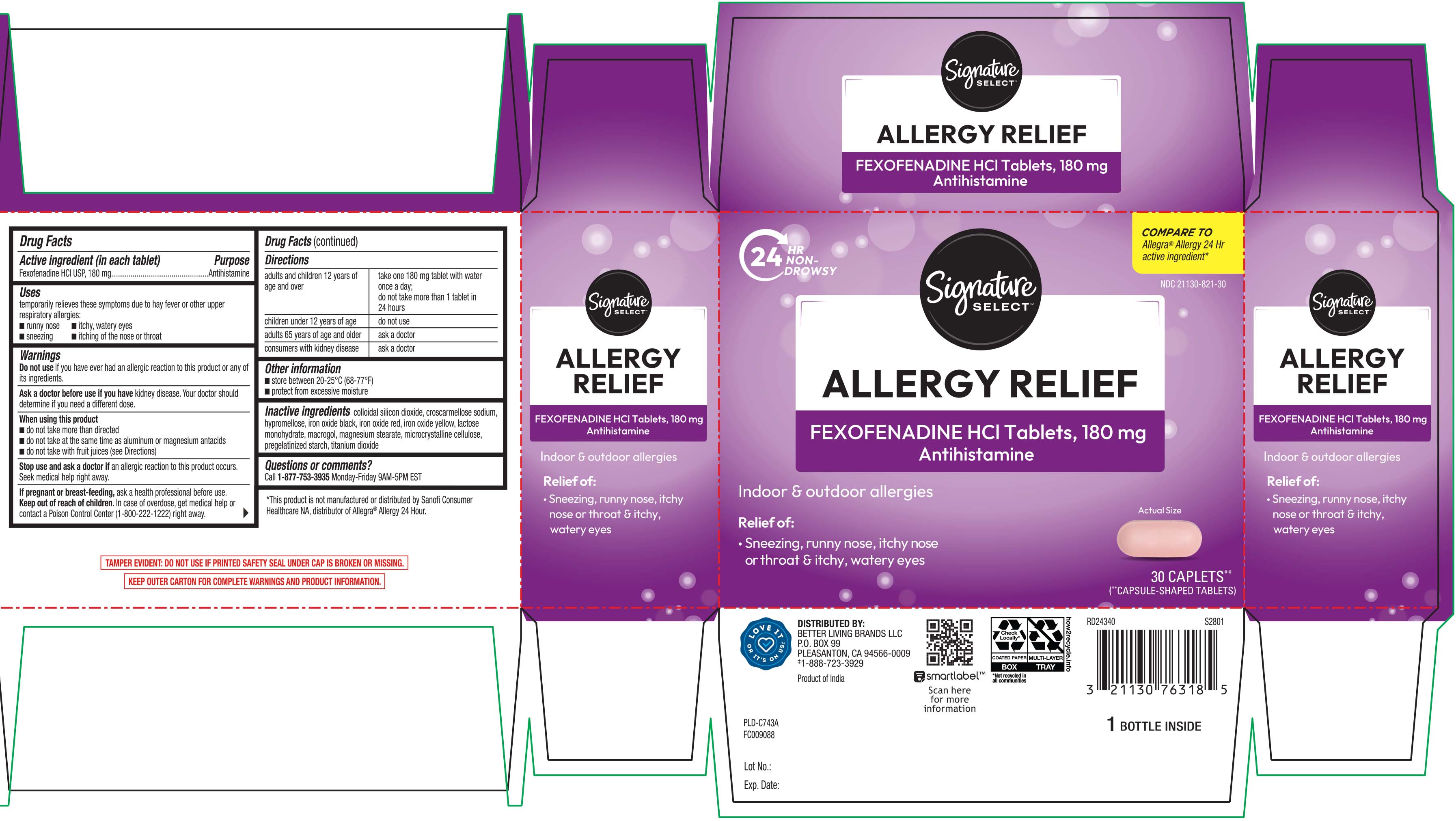 DRUG LABEL: Allergy Relief
NDC: 21130-821 | Form: TABLET
Manufacturer: Safeway, Inc.
Category: otc | Type: HUMAN OTC DRUG LABEL
Date: 20260126

ACTIVE INGREDIENTS: FEXOFENADINE HYDROCHLORIDE 180 mg/1 1
INACTIVE INGREDIENTS: SILICON DIOXIDE; CROSCARMELLOSE SODIUM; HYPROMELLOSES; FERRIC OXIDE RED; FERRIC OXIDE YELLOW; LACTOSE MONOHYDRATE; POLYETHYLENE GLYCOL, UNSPECIFIED; TITANIUM DIOXIDE; ANHYDROUS LACTOSE; STARCH, CORN; FERROSOFERRIC OXIDE; MAGNESIUM STEARATE

DRUG FACTS

Active ingredient (in each tablet)

Fexofenadine HCl USP 180 mg

Purpose

Antihistamine

Uses

temporarily relieves these symptoms due to hay fever or other upper respiratory allergies:

- runny nose
- itchy, watery eyes
- sneezing
- itching of the nose or throat

Warnings

Do not use

if you have ever had an allergic reaction to this product or any of its ingredients.

Ask a doctor before use if you have

kidney disease. Your doctor should determine if you need a different dose.

When using this product

- do not take more than directed
- do not take at the same time as aluminum or magnesium antacids
- do not take with fruit juices (see Directions)

Stop use and ask a doctor if

an allergic reaction to this product occurs. Seek medical help right away.

If pregnant or breast-feeding,

ask a health professional before use.

Keep out of reach of children.

In case of overdose, get medical help or contact a Poison Control Center (1-800-222-1222) right away

Directions

adults and children 12 years of age and over | take one 18 mg tablet with water once a day;; do not take more than 1 tablet in 24 hours
children under 12 years of age | do not use
adults 65 years of age and older | ask a doctor
consumers with kidney disease | ask a doctor

Other information

- store between 20-25ºC (68-77ºF)
- protect from excessive moisture

Inactive ingredients

colloidal silicon dioxide, croscarmellose sodium, hypromellose, iron oxide black, iron oxide red, iron oxide yellow, lactose monohydrate, macrogol, magnesium stearate, microcrystalline cellulose, pregelatinized starch (maize), titanium dioxide,

Questions or comments?

call 1-877-753-3935 Monday-Friday 9AM-5PM EST

Principal Display Panel

COMPARE TO Allegra® Allergy 24 Hr active ingredient*

24 Hour

Allergy Relief

FEXOFENADINE HCI 180mg

Antihistamine Tablets

- Relief of: Runny nose, sneezing, itchy, watery eyes, itchy nose or throat
- For indoor and outdoor allergies
- Non-drowsy

CAPLETS**

(**Capsule-shaped tablets)

*This product is not manufactured or distributed by Chattem Inc., distributor of Allegra® Allergy 24 HR.

TAMPER EVIDENT: DO NOT USE IF PRINTED SAFETY SEAL UNDER CAP IS BROKEN OR MISSING.

KEEP OUTER CARTON FOR COMPLETE WARNINGS AND PRODUCT INFORMATION

DISTRIBUTED BY:

BETTER LIVING BRANDS LLC

P.O. BOX, PLEASANT, CA 94566-0009

www.betterlivingbrandsLLC.com

Product Label

Signature Select Fexofenadine HCl Tablets, 180 mg